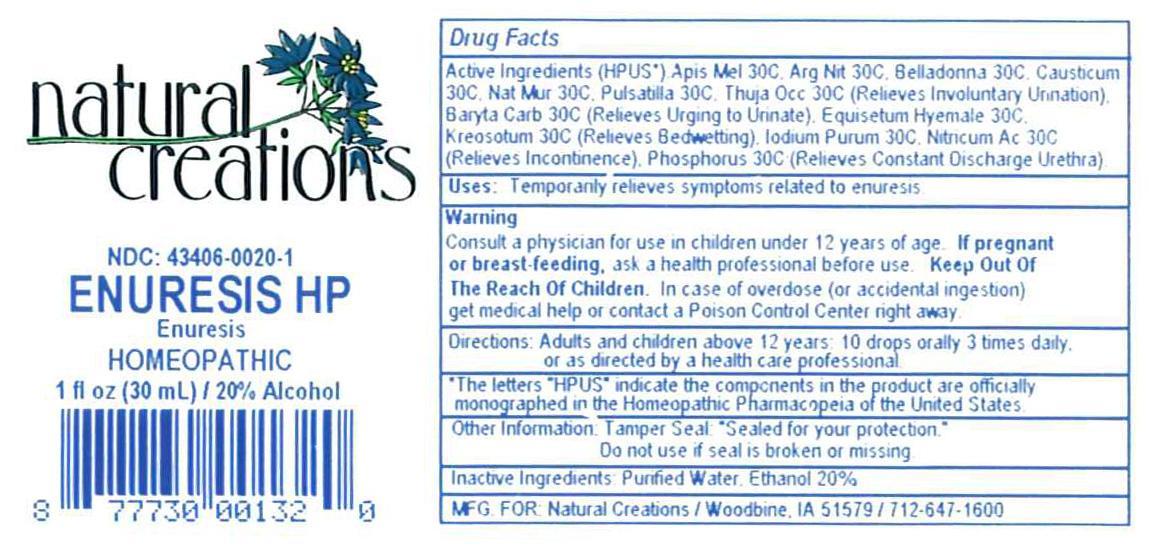 DRUG LABEL: ENURESIS HP
NDC: 43406-0020 | Form: LIQUID
Manufacturer: Natural Creations, Inc.
Category: homeopathic | Type: HUMAN OTC DRUG LABEL
Date: 20121101

ACTIVE INGREDIENTS: APIS MELLIFERA 30 [hp_C]/1 mL; SILVER NITRATE 30 [hp_C]/1 mL; BARIUM CARBONATE 30 [hp_C]/1 mL; ATROPA BELLADONNA 30 [hp_C]/1 mL; CAUSTICUM 30 [hp_C]/1 mL; EQUISETUM HYEMALE 30 [hp_C]/1 mL; IODINE 30 [hp_C]/1 mL; WOOD CREOSOTE 30 [hp_C]/1 mL; SODIUM CHLORIDE 30 [hp_C]/1 mL; NITRIC ACID 30 [hp_C]/1 mL; PHOSPHORUS 30 [hp_C]/1 mL; PULSATILLA VULGARIS 30 [hp_C]/1 mL; THUJA OCCIDENTALIS LEAFY TWIG 30 [hp_C]/1 mL
INACTIVE INGREDIENTS: WATER; ALCOHOL

ENURESIS HP

ACTIVE INGREDIENT

ACTIVE INGREDIENTS (HPUS*): Apis Mellifica 30C, Argentum Nitricum 30C, Baryta Carbonica 30C, Belladonna 30C, Causticum 30C, Equisetum Hyemale 30C, Iodium Purum 30C, Kreosotum 30C, Natrum Muriaticum 30C, Nitricum Acidum 30C, Phosphorus 30C, Pulsatilla 30C, Thuja Occidentalis 30C

INDICATIONS AND USAGE

USES: Temporarily relieves involuntary urination, urging to urinate, bedwetting, incontinence, &/or other symptoms related to enuresis.

WARNING:

Consult a physician for use inc hildren under 12 years of age. IF PREGNANT OR BREAST-FEEDING, ask a health care professional before use. KEEP OUT OF THE REACH OF CHILDREN. In case of overdose (or accidental ingestion) get medical help or contact a Poison Control Center right away.

DOSAGE AND ADMINISTRATION

DIRECTIONS: Adults and children above 12 yeears: 10 drops orally 3 times daily, or as directed by a health care professional.

OTHER INFORMATION: Tamper Seal: "Sealed for your protection."

Do not use if seal is broken or missing.

REFERENCES

n the product are officially monographed in the Homeopathic Pharmacopeia of the United States.

INACTIVE INGREDIENTS: Purified Water, USP Ethanol Alcohol 20%

QUESTIONS AND COMMENTS?
MFG FOR: Natural Creations / Woodbine, IA / 51579 712.647.1600

PURPOSE

USES: Temporarily relieves involuntary urination, urging to urinate, bedwetting, incontinence, &/or other symptoms related to enuresis.

PACKAGE LABEL

NDC: 43406-0020-1

ENURESIS HP

Enuresis

HOMEOPATHIC
1 fl oz (30 mL) / 20% Alcohol

UPC: 877730001320